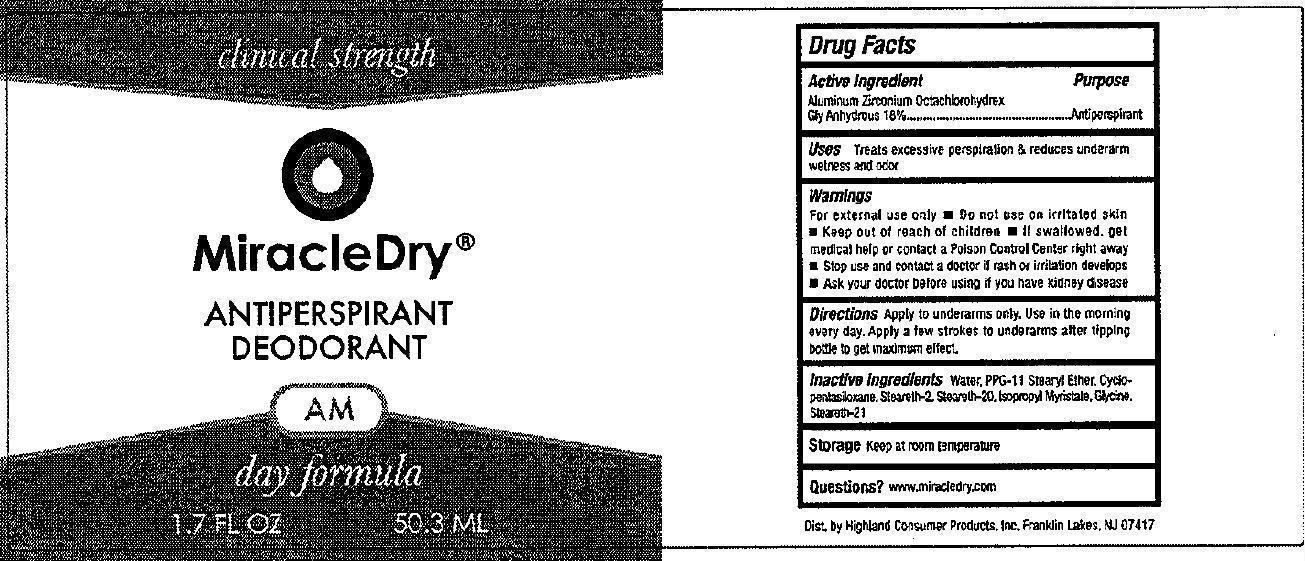 DRUG LABEL: Clinical Strength MiracleDry Antiperspirant Deodorant AM
NDC: 53897-000 | Form: LIQUID
Manufacturer: Highland Consumer Products
Category: otc | Type: HUMAN OTC DRUG LABEL
Date: 20231214

ACTIVE INGREDIENTS: ALUMINUM ZIRCONIUM OCTACHLOROHYDREX GLY 18 mg/1 mL
INACTIVE INGREDIENTS: WATER; PPG-11 STEARYL ETHER; CYCLOMETHICONE 5; STEARETH-2; STEARETH-20; ISOPROPYL MYRISTATE; GLYCINE; STEARETH-21

Clinical Strength MiracleDry Antiperspirant Deodorant AM

Active Ingredient

Aluminum Zirconium Octachlorohydrex Gly Anhydrous 18%

PURPOSE

Antiperspirant

Uses

Treats excessive perspiration and reduces underarm wetness and odor.

Warnings

For external use only

Do not use

on irritated skin.

Keep out of reach of children

If swallowed, get medical help or contact a Poison Control Center right away

Stop use and contact a doctor

if rash or irritation develops

Ask your doctor

before using if you have kidney disease

Directions

Apply to underarms only. Use in the morning every day. Apply few strokes to underarms after tipping bottle to get maximum effect.

Inactive Ingredients

Water, PPG-11 Stearyl Ether, Cyclopentasiloxane, Steareth-2, Steareth-20, Isopropyl Myristate, Glycine, Steareth-21

Storage

Keep at room temperature

Questions?

www.miracledry.com

PACKAGE LABEL

clinical strength Miracle Dry ANTIPERSPIRANT DEODORANT AM day formula 1.7 FL OZ 50.3 ML